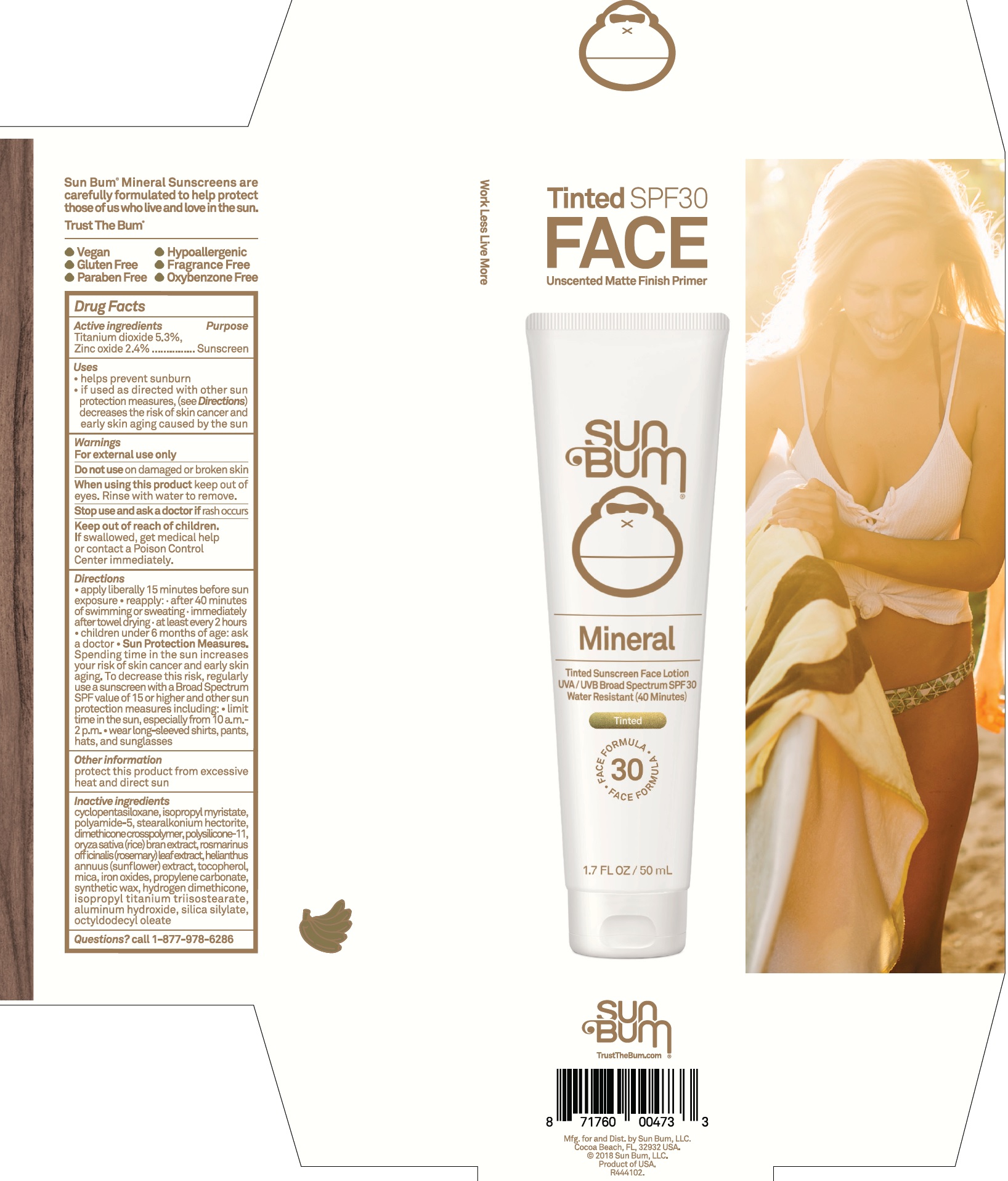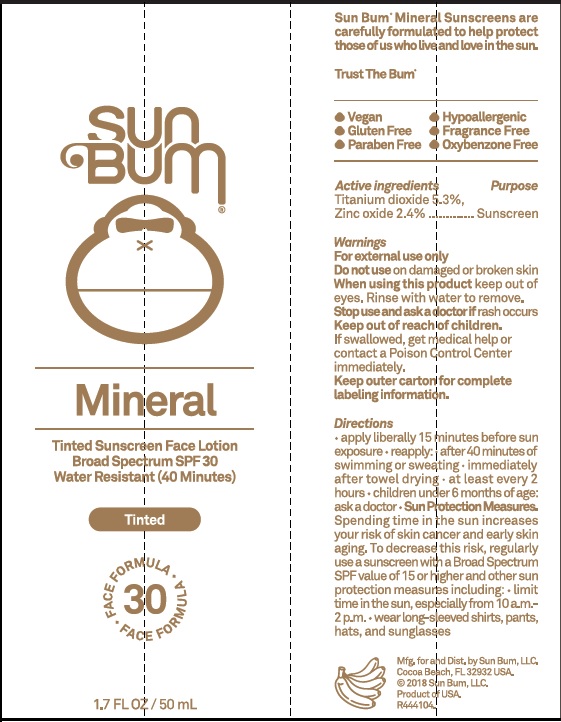 DRUG LABEL: Sun Bum Mineral SPF 30 Tinted Sunscreen Face
NDC: 69039-258 | Form: LOTION
Manufacturer: Sun Bum LLC
Category: otc | Type: HUMAN OTC DRUG LABEL
Date: 20220204

ACTIVE INGREDIENTS: TITANIUM DIOXIDE 53 mg/1 mL; ZINC OXIDE 24 mg/1 mL
INACTIVE INGREDIENTS: CYCLOMETHICONE 5; ISOPROPYL MYRISTATE; STEARALKONIUM HECTORITE; DIMETHICONE CROSSPOLYMER (450000 MPA.S AT 12% IN CYCLOPENTASILOXANE); DIMETHICONE/VINYL DIMETHICONE CROSSPOLYMER (SOFT PARTICLE); RICE BRAN; ROSEMARY; HELIANTHUS ANNUUS FLOWERING TOP; TOCOPHEROL; MICA; FERRIC OXIDE RED; PROPYLENE CARBONATE; ISOPROPYL TITANIUM TRIISOSTEARATE; ALUMINUM HYDROXIDE; OCTYLDODECYL OLEATE

Sun Bum Mineral SPF 30 Tinted Sunscreen Face Lotion

Active ingredients

Titanium dioxide 5.3%

Zinc oxide 2.4%

Purpose

Sunscreen

Uses

• helps prevent sunburn

• if used as directed with other sun protection measures (see Directions), decreases the risk of skin cancer and early skin aging caused by the sun

Warnings

For external use only

Do not use

on damaged or broken skin

When using this product

keep out of eyes. Rinse with water to remove.

Stop use and ask a doctor

if rash occurs

Keep out of reach of children.

If swallowed, get medical help or contact a Poison Control Center immediately.

Directions

• apply liberally 15 minutes before sun exposure • reapply: • after 40 minutes of swimming or sweating • immediately after towel drying • at least every 2 hours • children under 6 months of age: ask a doctor • Sun Protection Measures. Spending time in the sun increases your risk of skin cancer and early skin aging. To decrease this risk, regularly use a sunscreen with a Broad Spectrum SPF value of 15 or higher and other sun protection measures including: • limit time in the sun, especially from 10 a.m.-2 p.m. • wear long-sleeved shirts, pants, hats, and sunglasses

Other information

protect this product from excessive heat and direct sun

Inactive ingredients

cyclopentasiloxane, isopropyl myristate, polyamide-5, stearalkonium hectorite, dimethicone crosspolymer, polysilicone 11, oryza sativa (rice) bran extract, rosmarinus officinalis (rosemary) leaf extract, helianthus annuus (sunflower) extract, tocopherol, mica, iron oxides, propylene carbonate, synthetic wax, hydrogen dimethicone, isopropyl titanium triisostearate, aluminum hydroxide, silica silylate, octyldodecyl oleate

Questions?

call 1-877-978-6286